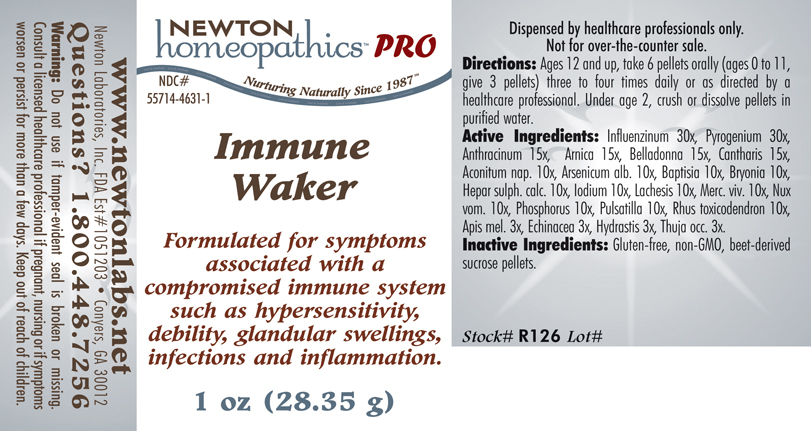 DRUG LABEL: Immune Waker 
NDC: 55714-4631 | Form: PLASTER
Manufacturer: Newton Laboratories, Inc.
Category: homeopathic | Type: HUMAN PRESCRIPTION DRUG LABEL
Date: 20131230

ACTIVE INGREDIENTS: Influenza A Virus 30 [hp_X]/1 g; Rancid Beef 30 [hp_X]/1 g; Bacillus Anthracis Immunoserum Rabbit 15 [hp_X]/1 g; Arnica Montana 15 [hp_X]/1 g; Atropa Belladonna 15 [hp_X]/1 g; Lytta Vesicatoria 15 [hp_X]/1 g; Aconitum Napellus 10 [hp_X]/1 g; Arsenic Trioxide 10 [hp_X]/1 g; Baptisia Tinctoria Root 10 [hp_X]/1 g; Bryonia Alba Root 10 [hp_X]/1 g; Calcium Sulfide 10 [hp_X]/1 g; Iodine 10 [hp_X]/1 g; Lachesis Muta Venom 10 [hp_X]/1 g; Mercury 10 [hp_X]/1 g; Strychnos Nux-vomica Seed 10 [hp_X]/1 g; Phosphorus 10 [hp_X]/1 g; Pulsatilla Vulgaris 10 [hp_X]/1 g; Toxicodendron Pubescens Leaf 10 [hp_X]/1 g; Apis Mellifera 3 [hp_X]/1 g; Echinacea, Unspecified 3 [hp_X]/1 g; Goldenseal 3 [hp_X]/1 g; Thuja Occidentalis Leafy Twig 3 [hp_X]/1 g; Influenza B Virus 30 [hp_X]/1 g
INACTIVE INGREDIENTS: Sucrose

Immune Waker

INDICATIONS & USAGE SECTION

Formulated for symptoms associated with a compromised immune system such as hypersensitivity, debility, glandular swellings, infections and inflammation.

DOSAGE & ADMINISTRATION SECTION

Directions: Ages 12 and up, take 6 pellets orally (ages 0 to11, give 3 pellets) three to four times daily or as directed by a healthcare professional. Under age 2, crush or dissolve pellets in purified water.

ACTIVE INGREDIENT SECTION

Influenzinum 30x, Pyrogenium 30x, Anthracinum 15x, Arnica 15x, Belladonna 15x, Cantharis 15x, Aconitum nap. 10x, Arsenicum alb.10x, Baptisia 10x, Bryonia 10x, Hepar sulph. calc. 10x, Iodium 10x, Lachesis 10x, Merc. viv. 10x, Nux vom. 10x, Phosphorus 10x, Pulsatilla 10x, Rhus toxicodendron 10x, Apis mel. 3x, Echinacea 3x, Hydrastis 3x, Thuja occ. 3x.

PURPOSE SECTION

Formulated for symptoms associated with a compromised immune system such as hypersensitivity, debility, glandular swellings, infections and inflammation.

INACTIVE INGREDIENT SECTION

Inactive Ingredients: Gluten-free, non-GMO, beet-derived sucrose pellets.

QUESTIONS SECTION

www.newtonlabs.net Newton Laboratories, Inc. FDA Est # 1051203 - Conyers, GA 30012 Questions? 1.800.448.7256

WARNINGS SECTION

Warning: Do not use if tamper - evident seal is broken or missing. Consult a licensed healthcare professional if pregnant, nursing or if symptoms worsen or persist for more than a few days. Keep out of reach of children.

PREGNANCY OR BREAST FEEDING SECTION

Consult a licensed healthcare professional if pregnant, nursing or if symptoms worsen or persist for more than a few days.

KEEP OUT OF REACH OF CHILDREN SECTION

Keep out of reach of children.